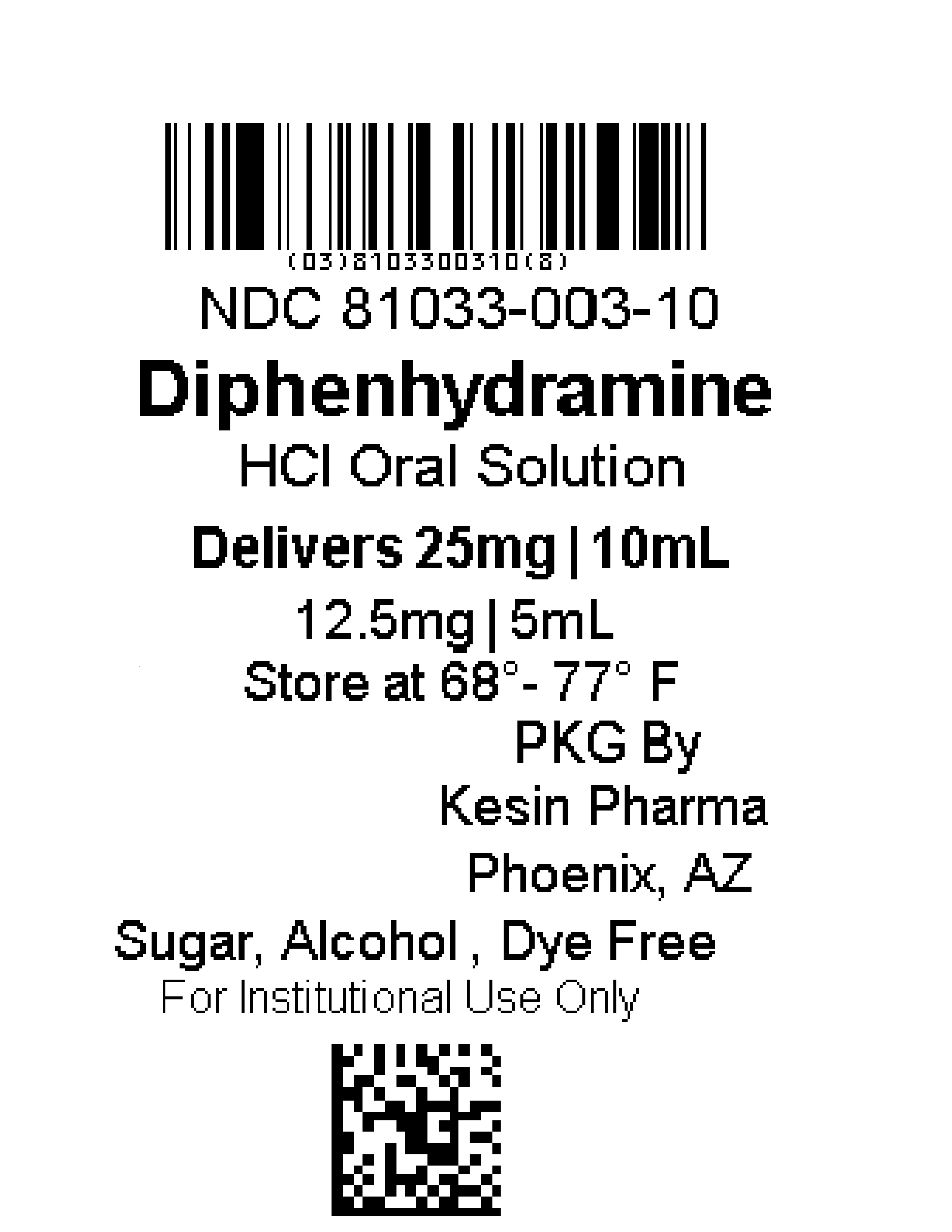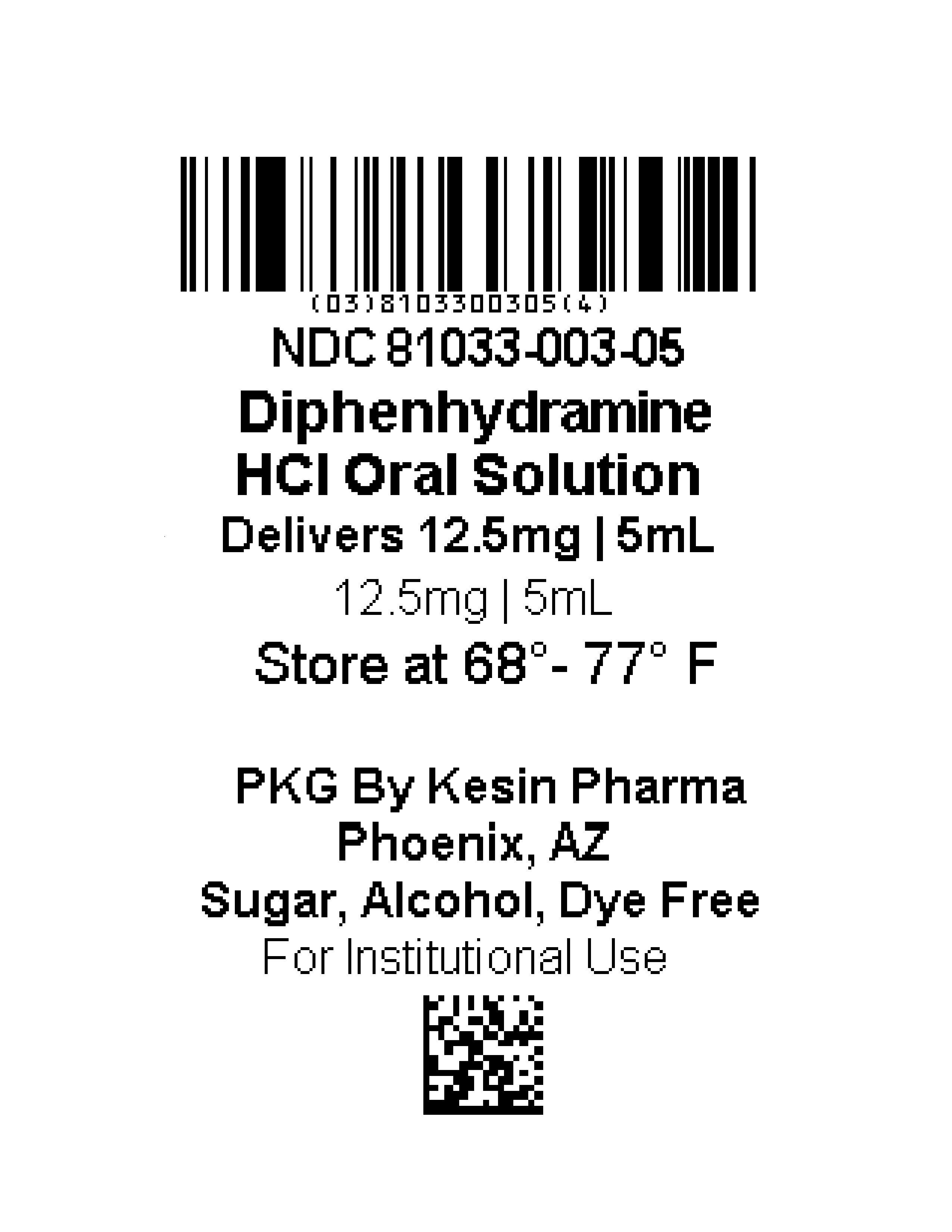 DRUG LABEL: Diphenhydramine Hydrochloride
NDC: 81033-003 | Form: LIQUID
Manufacturer: Kesin Pharma Corporation
Category: otc | Type: HUMAN OTC DRUG LABEL
Date: 20230116

ACTIVE INGREDIENTS: DIPHENHYDRAMINE HYDROCHLORIDE 2.5 mg/1 mL
INACTIVE INGREDIENTS: TRISODIUM CITRATE DIHYDRATE; WATER; SORBITOL; SUCRALOSE; XANTHAN GUM; CITRIC ACID MONOHYDRATE; GLYCERIN; PROPYLENE GLYCOL; SODIUM BENZOATE

Diphenhydramine HCl 2.5mg/mL Unit Dose Cups, 12.5mg/5 mL, 25mg/10mL

ACTIVE INGREDIENT (in each 5 mL)

Diphenhydramine HCl 12.5mg

PURPOSE

Antihistamine

USES

For the temporary relief of runny nose, sneezing, itching of the nose or throat, and itchy, watery eyes due to hay fever or other upper respiratory allergies or allergic rhinitis.

WARNINGS

Do not use

• to make a child sleepy

• with any other product containing diphenhydramine, even one used on skin

• this product, unless directed by a doctor, if you have a breathing problem such as emphysema or chronic bronchitis, or if you have glaucoma or difficulty in urination due to enlargement of the prostate gland

Ask a doctor before use if your child has

• a breathing problem such as chronic bronchitis

• glaucoma

• a sodium-restricted diet

Ask a doctor or pharmacist before use if the child is

• taking sedatives or tranquilizers

When using this product

• marked drowsiness may occur

• sedatives and tranquilizers may increase drowsiness

• excitability may occur, especially in children

• avoid alcoholic beverages while taking this product. Do not take this product if you are taking sedatives or tranquilizers, without first consulting your doctor. Use caution when driving a motor vehicle or operating machinery.

Keep our of reach of children

In case of overdose, get medical help or contact a Poison Control Center right away (1-800-222-1222).

DIRECTIONS

Adults and children 12 years of age and over: oral dosage is 25 to 50 milligrams every 4 to 6 hours, not to exceed 300 milligrams in 24 hours, or as directed by a doctor.

Children 6 to under 12 years of age: oral dosage is 12.5 to 25 milligrams every 4 to 6 hours, not to exceed 150 milligrams in 24 hours, or as directed by a doctor. Children under 6 years of age: consult a doctor.

OTHER INFORMATION

• each 5 mL contains: 16mg of sodium

• store at 20°-25°C (68°-77°F)

• tamper evident: DO NOT use if foil on cup is missing or torn

• Alcohol Free, Dye Free, Sugar Free

• NDC 81033-003-05 (12.5mg) unit dose cup

• NDC 81033-003-10 (25 mg) unit dose cup

INACTIVE INGREDIENTS

citric acid, glycerin, propylene glycol, water, sodium benzoate, sorbitol, sucralose, trisodium citrate dihydrate, xanthan gum, mixed berry flavor, strawberry flavor

QUESTIONS or COMMENTS?

Call 1-833-537-4679

HOW SUPPLIED

• NDC 81033-003-05 (12.5mg) unit dose cup

• NDC 81033-003-10 (25 mg) unit dose cup

PRINCIPAL DISPLAY PANEL

[ Barcode]

NDC 81033-003-05

Diphenhydramine

HCl Oral Solution

Delivers 12.5mg / 5 mL

12.5mg / 5 mL

Store at 68° - 77° F

[ Lot # Exp Date]

PKG by Kesin Pharma

Phoenix, AZ

Sugar, Alcohol, Dye Free

For Institutional Use Only

[Barcode]

[Barcode]

NDC 81033-003-10

Diphenhydramine

HCl Oral Solution

Delivers 25mg / 10 mL

12.5mg / 5 mL

Store at 68° - 77° F

[Lot #] PKG by

[Exp Date] Kesin Pharma

Phoenix, AZ

Sugar, Alcohol, Dye Free

For Institutional Use Only

[Barcode]